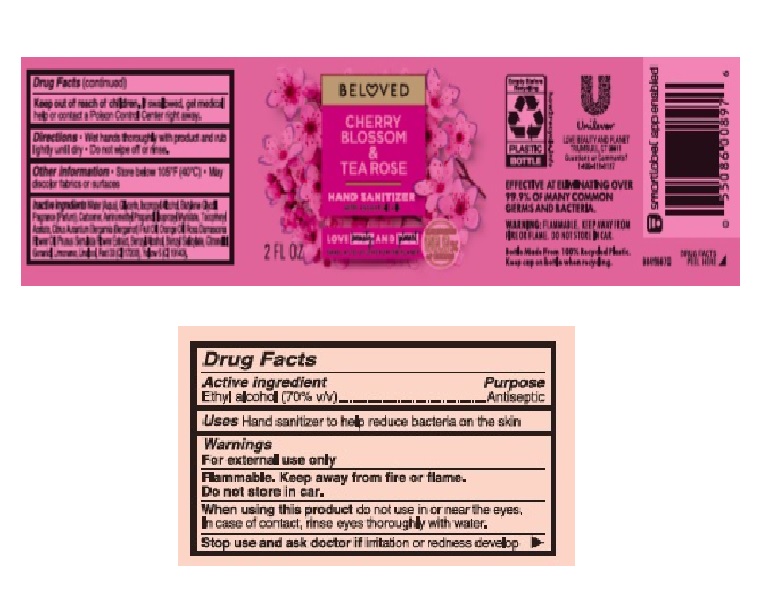 DRUG LABEL: Love Beauty and Planet
NDC: 64942-1841 | Form: GEL
Manufacturer: Conopco Inc. d/b/a/ Unilever
Category: otc | Type: HUMAN OTC DRUG LABEL
Date: 20241107

ACTIVE INGREDIENTS: ALCOHOL 700 mg/1 mL
INACTIVE INGREDIENTS: BENZYL SALICYLATE; LIMONENE, (+)-; LINALOOL, (+/-)-; BUTYLENE GLYCOL; BERGAMOT OIL; ISOPROPYL ALCOHOL; ORANGE OIL; .ALPHA.-TOCOPHEROL ACETATE; CARBOMER HOMOPOLYMER, UNSPECIFIED TYPE; D&C RED NO. 33; AMINOMETHYLPROPANOL; WATER; GLYCERIN; ISOPROPYL MYRISTATE; .BETA.-CITRONELLOL, (R)-; FD&C YELLOW NO. 5; ROSA DAMASCENA FLOWER OIL; PRUNUS SERRULATA FLOWER; BENZYL ALCOHOL; GERANIOL

Love Beauty and Planet Beloved Cherry Blossom & Tea Rose Hand Sanitizer

LOVE BEAUTY AND PLANET BELOVED CHERRY BLOSSOM & TEA ROSE HAND SANITIZER - Ethyl Alcohol gel

Love Beauty and Planet Beloved Cherry Blossom & Tea Rose Hand Sanitizer

Drug Facts

Active ingredient

Ethyl Alcohol 70 %

Purpose

Antiseptic

Uses

Hand sanitizer to help reduce bacteria on the skin

Warnings

For external use only
Flammable. Keep away from fire or flame. Do not store in car .
When using this product do not use in or near the eyes.
Stop use and ask doctor if irritation or redness develop.

• Keep out of reach of children except under adult supervision.

If swallowed, get medical help or contact a Poison Control Center right away.

Directions

Wet hands thoroughly with product and rub lightly until dry. Do not wipe off or rinse.

Other information

Store below 105˚F (40˚C). May discolor fabrics or surfaces.

Inactive ingredients

Water (Aqua), Glycerin, Isopropyl Alcohol, Butylene Glycol, Fragrance (Parfum), Carbomer, Aminomethyl Propanol, Isopropyl Myristate, Tocopheryl Acetate, Citrus Aurantium Bergamia (Bergamot) Fruit Oil, Orange Oil, Rosa Damascena Flower Oil, Prunus Serrulata Flower Extract, Benzyl Alcohol, Benzyl Salicylate, Citronellol, Geraniol, Limonene, Linalool, Red 33 (CI 17200), Yellow 5 (CI 19140).

Questions or comments?

1-800-418-3137